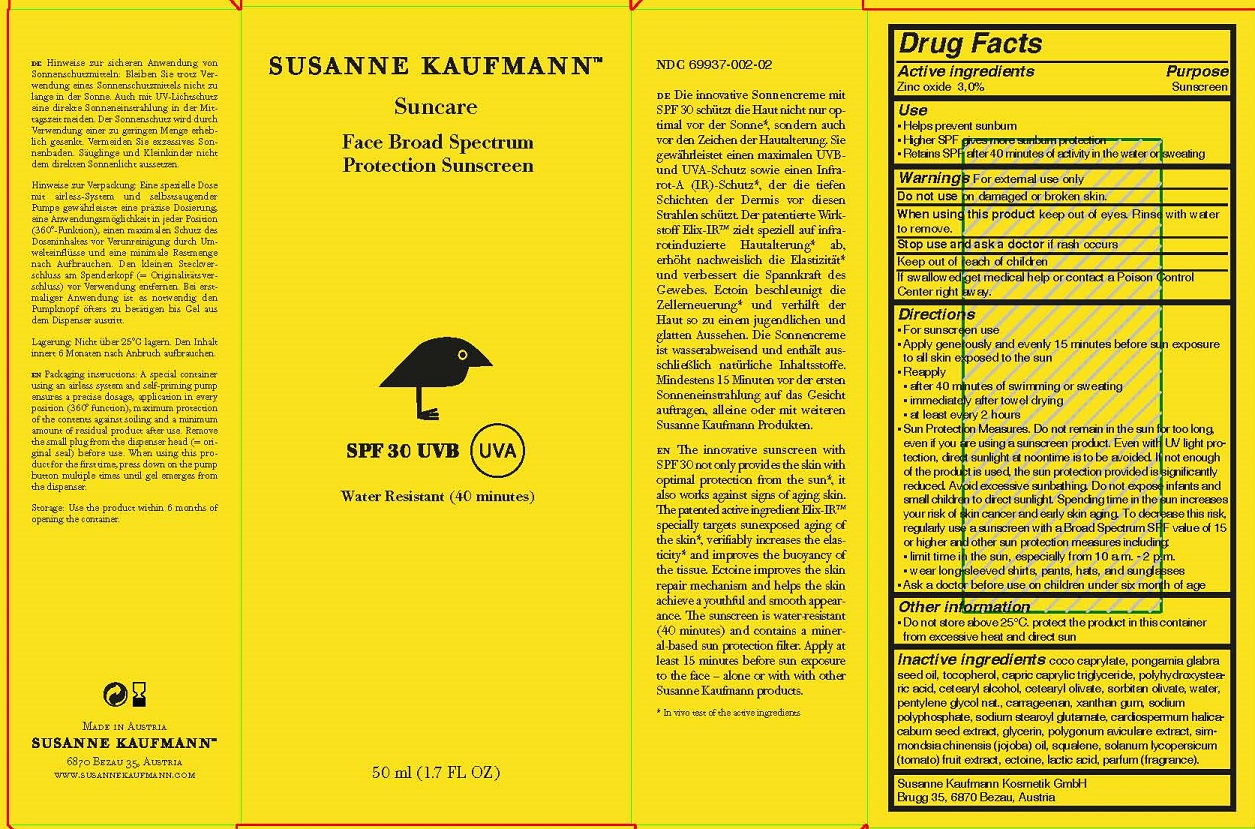 DRUG LABEL: SUSANNE KAUFMANN SUNCARE FACE BROAD SPECTRUM PROTECTION SUNSCREEN
NDC: 69937-002 | Form: LOTION
Manufacturer: Susanne Kaufmann Kosmetik GmbH
Category: otc | Type: HUMAN OTC DRUG LABEL
Date: 20170716

ACTIVE INGREDIENTS: ZINC OXIDE 30 mg/1 mL
INACTIVE INGREDIENTS: SQUALENE; TOMATO; ECTOINE; LACTIC ACID; COCO-CAPRYLATE; CARRAGEENAN; XANTHAN GUM; SODIUM POLYMETAPHOSPHATE; SODIUM STEAROYL GLUTAMATE; MEDIUM-CHAIN TRIGLYCERIDES; POLYHYDROXYSTEARIC ACID (2300 MW); CETOSTEARYL ALCOHOL; CETEARYL OLIVATE; PENTYLENE GLYCOL; GLYCERIN; POLYGONUM AVICULARE TOP; CARDIOSPERMUM HALICACABUM SEED; WATER; KARUM SEED OIL; TOCOPHEROL; SORBITAN OLIVATE; JOJOBA OIL

ACTIVE INGREDIENT

Zinc oxide 3.0%

PURPOSE

Sunscreen

INDICATIONS AND USAGE

- Helps prevent sunburn
- Higher SPF gives more sunburn protection
- Retains SPF after 40 minutes of activity in the water or sweating

WARNINGS

For external use only

Do not use on damaged or broken skin.

When using this product keep out of eyes. Rinse with water to remove.

Stop use and ask a doctor if rash occurs

Keep out of reach of children

If swallowed get medical help or contact a Poison Control Center right away.

DOSAGE AND ADMINISTRATION

- For sunscreen use
- Apply generously and evenly 15 minutes before sun exposure to all skin exposed to the sun
- Reapply
- after 40 minutes of swimming or sweating
- immediately after towel drying
- at least every 2 hours
- Sun Protection Measures. Do not remain in the sun for too long, even if you are using a sunscreen product. Even with UV light protection, direct sunlight at noontime is to be avoided. If not enough of the product is used, the sun protection provided is significantly reduced. Avoid excessive sunbathing. Do not expose infants and small children to direct sunlight. Spending time in the sun increases your risk of skin cancer and early skin aging. To decrease this risk, regularly use a sunscreen with a Broad Spectrum SPF value of 15 or higher and other sun protection measures including:
- limit time in the sun, especially from 10 a.m. - 2 p.m.
- wear long-sleeved shirts, pants, hats, and sunglasses
- Ask a doctor before use on children under six month of age

OTHER SAFETY INFORMATION

Do not store above 25°C. protect the product in this container from excessive heat and direct sun

INACTIVE INGREDIENT

coco caprylate, pongamia glabra seed oil, tocopherol, capric caprylic triglyceride, polyhydroxystearic acid, cetearyl alcohol, cetearyl olivate, sorbitan olivate, water, pentylene glycol nat., carrageenan, xanthan gum, sodium polyphosphate, sodium stearoyl glutamate, cardiospermum halicacabum seed extract, glycerin, polygonum aviculare extract, simmondsia chinensis (jojoba) oil, squalene, solanum lycopersicum (tomato) fruit extract, ectoine, lactic acid, parfum (fragrance).